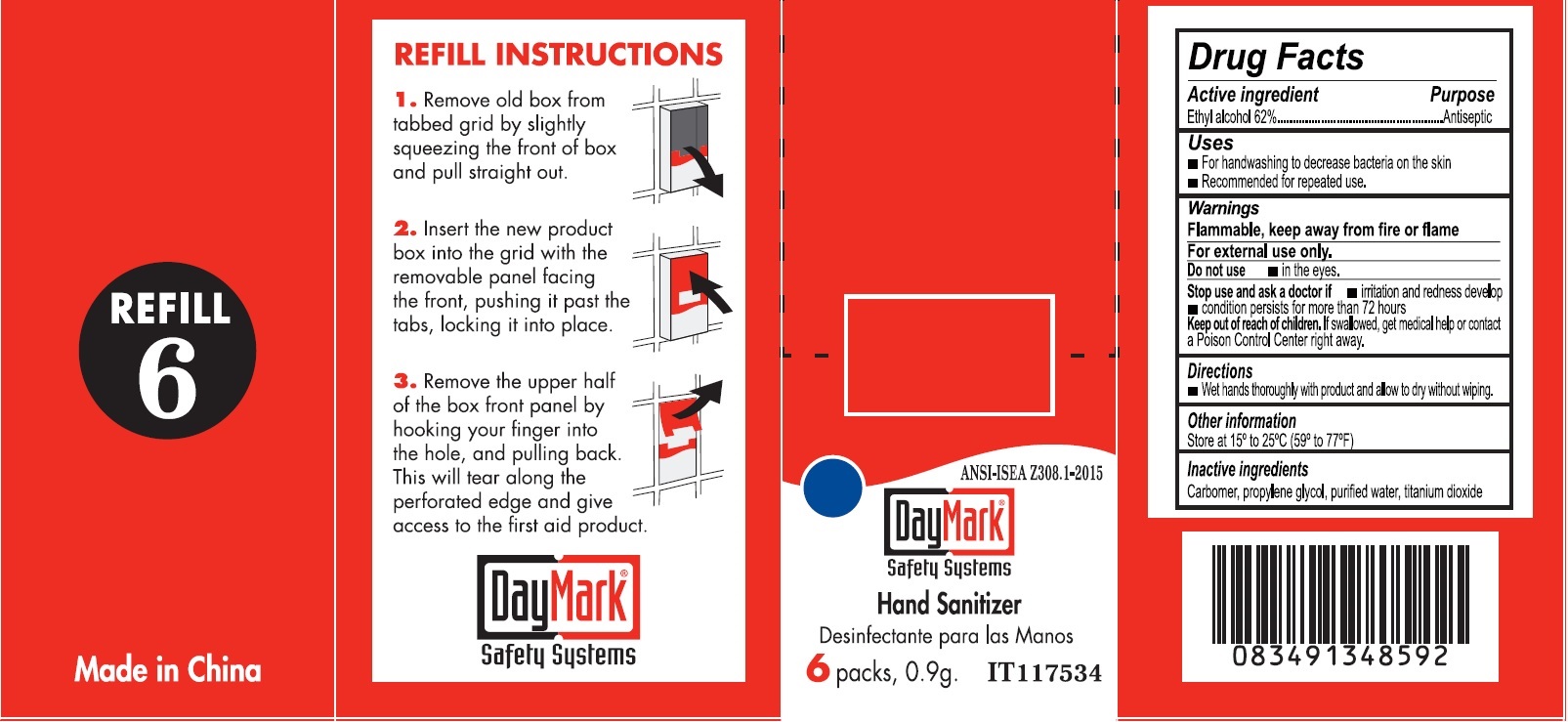 DRUG LABEL: Hand Sanitizer
NDC: 49687-0015 | Form: GEL
Manufacturer: CMC Group Inc.
Category: otc | Type: HUMAN OTC DRUG LABEL
Date: 20250113

ACTIVE INGREDIENTS: ALCOHOL 0.62 g/1 g
INACTIVE INGREDIENTS: CARBOXYPOLYMETHYLENE; PROPYLENE GLYCOL; WATER; TITANIUM DIOXIDE

Hand Sanitizer

Active ingredient

Ethyl alcohol 62%

Purpose

Antiseptic

Uses

- For handwashing to decrease bacteria on the skin
- Recommended for repeated use.

Warnings

Flammable, keep away from fire or flame

For external use only.

Do not use

- in the eyes.

Stop use and ask a doctor if

- irritation and redness develop
- condition persists for more than 72 hours

Keep out of reach children.

If swallowed, get medical help or contact a Poison Control Center right away.

Directions

- Wet hands thoroughly with product and allow to dry without wiping.

Other information

Store at 15° to 25°C (59° to 77°F)

Inactive ingredients

Carbomer, propylene glycol, purified water, titanium dioxide